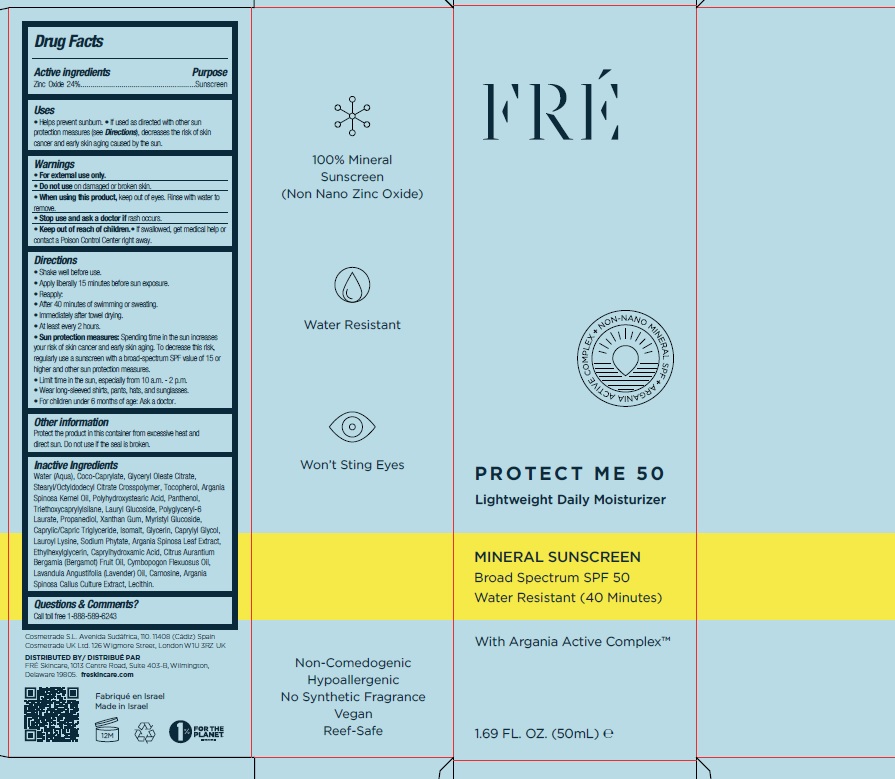 DRUG LABEL: Fre Protect Me Lightweight Daily Moisturizer SPF 50
NDC: 69435-1404 | Form: CREAM
Manufacturer: Peer Pharm Ltd.
Category: otc | Type: HUMAN OTC DRUG LABEL
Date: 20250213

ACTIVE INGREDIENTS: ZINC OXIDE 24 g/100 mL
INACTIVE INGREDIENTS: WATER; COCO-CAPRYLATE; GLYCERYL MONOOLEATE CITRATE; STEARYL/OCTYLDODECYL CITRATE CROSSPOLYMER; LAURYL GLUCOSIDE; XANTHAN GUM; PANTHENOL; PROPANEDIOL; POLYHYDROXYSTEARIC ACID (2300 MW); TRIETHOXYCAPRYLYLSILANE; ISOMALT; MEDIUM-CHAIN TRIGLYCERIDES; GLYCERIN; MYRISTYL GLUCOSIDE; CAPRYLYL GLYCOL; PHYTATE SODIUM; LAUROYL LYSINE; ARGANIA SPINOSA LEAF; CAPRYLHYDROXAMIC ACID; TOCOPHEROL; BERGAMOT OIL; EAST INDIAN LEMONGRASS OIL; LAVENDER OIL; CARNOSINE; ARGAN OIL; LECITHIN, SOYBEAN; ETHYLHEXYLGLYCERIN

Protect Me Lightweight Daily Moisturizer Mineral Sunscreen SPF 50

Active Ingredients

Zinc Oxide 24%

Purpose

Sunscreen

Uses

- Helps prevent sunburn
- if used as directed with other sun protection measures (see Directions), decreases the risk of skin cancer and early skin aging caused by the sun.

Warnings

- For external use only
- Do not use on damaged or broken skin.
- When using this product, Keep out of eyes. Rinse with water to remove.
- Stop use and ask a doctor if rash occurs

Keep out of reach of children.

If swallowed, call a Poison Control Center or get medical help right away.

Directions

• Shake well before use

- Apply liberally 15 minutes before sun exposure
- Reapply:
- After 40 minutes of swimming or sweating
- Immediately after towel drying
- At least every 2 hours
- Sun Protection MeasuresSpending time in the sun increases your risk of skin cancer and early skin aging. To decrease this risk, regularly use a sunscreen with a broad-spectrum SPF value of 15 or higher and other sun protection measures including:
- limit time in the sun, especially from 10a.m. to 2p.m.
- Wear long-sleeve shirts, pants, hats, and sunglasses.
- Children under 6 months: ask a doctor

Other information

Protect the product in this container from excessive heat and direct sun. Do not use if the seal is broken.

Inactive Ingredients

Water (Aqua), Coco-Caprylate, Glyceryl Oleate Citrate, Stearyl/Octyldodecyl Citrate Crosspolymer, Tocopherol, Argania Spinosa Kernel Oil, Polyhydroxystearic Acid, Panthenol, Triethoxycaprylylsilane, Lauryl Glucoside, Polyglyceryl-6 Laurate, Propanediol, Xanthan Gum, Myristyl Glucoside,Caprylic/Capric Triglyceride, Isomalt, Glycerin, Caprylyl Glycol, Lauroyl Lysine, Sodium Phytate, Argania Spinosa Leaf Extract,Ethylhexylglycerin, Caprylhydroxamic Acid, Citrus AurantiumBergamia (Bergamot) Fruit Oil, Cymbopogon Flexuosus Oil,Lavandula Angustifolia (Lavender) Oil, Carnosine, Argania Spinosa Callus Culture Extract, Lecithin.

Questions or Comments

Call toll free 1-888-589-6243